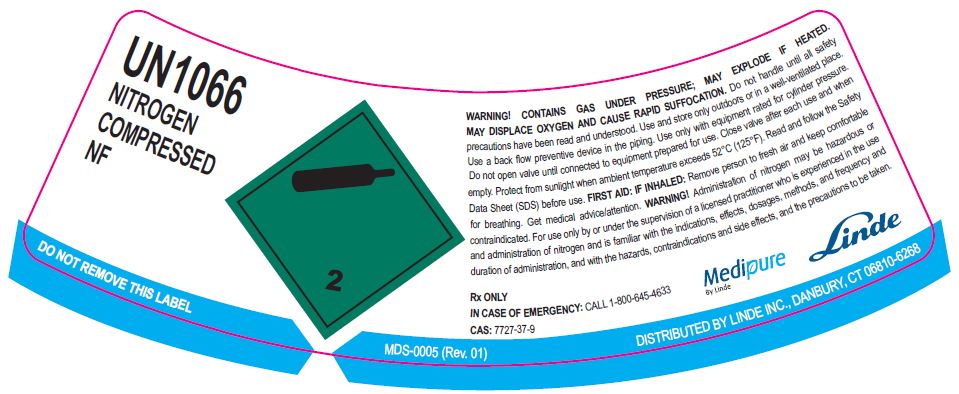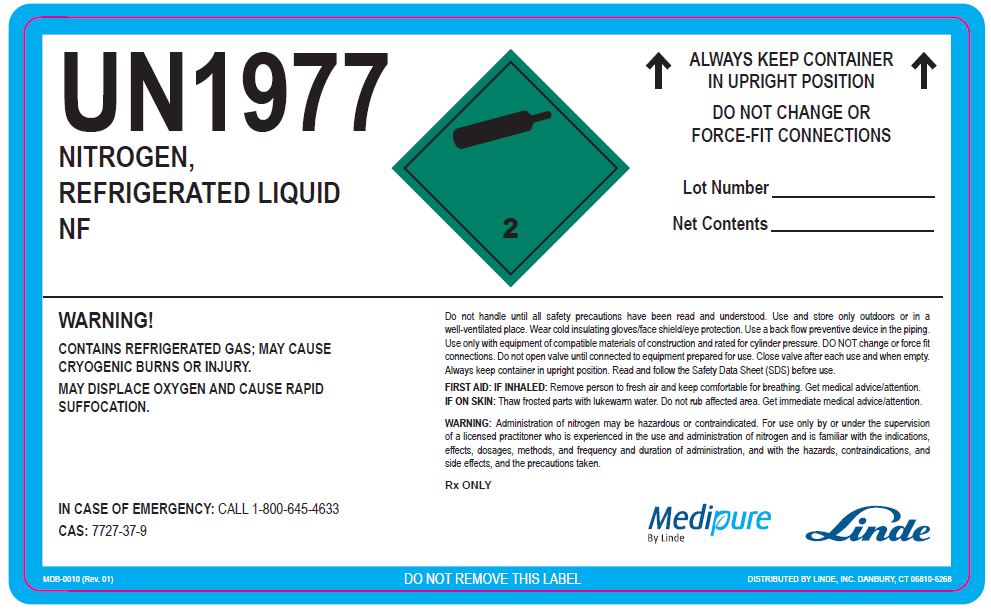 DRUG LABEL: Nitrogen
NDC: 11324-002 | Form: GAS
Manufacturer: Linde Puerto Rico B.V.
Category: prescription | Type: HUMAN PRESCRIPTION DRUG LABEL
Date: 20251231

ACTIVE INGREDIENTS: NITROGEN 990 mL/1 L

Nitrogen NF Gurabo